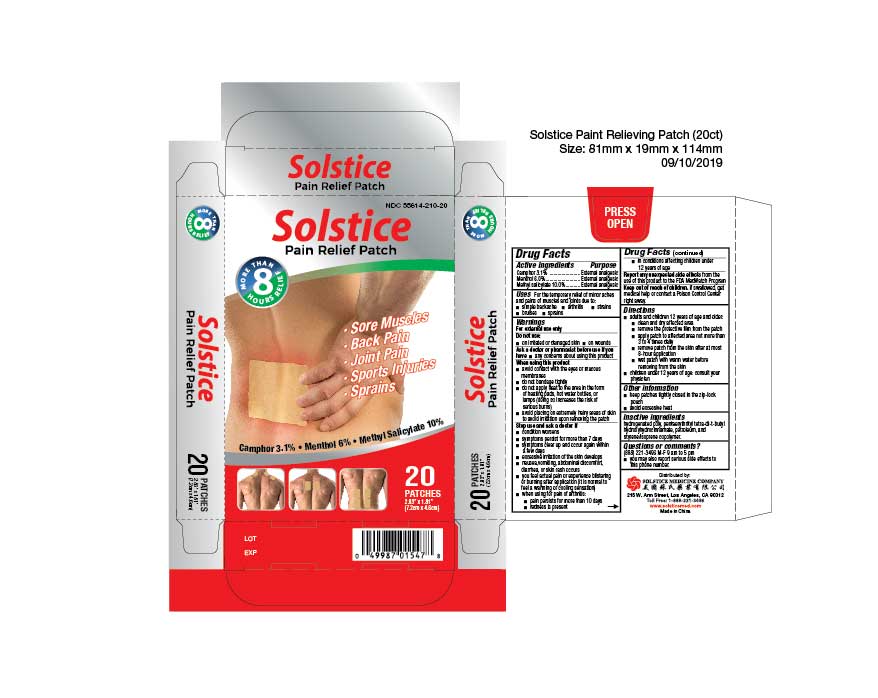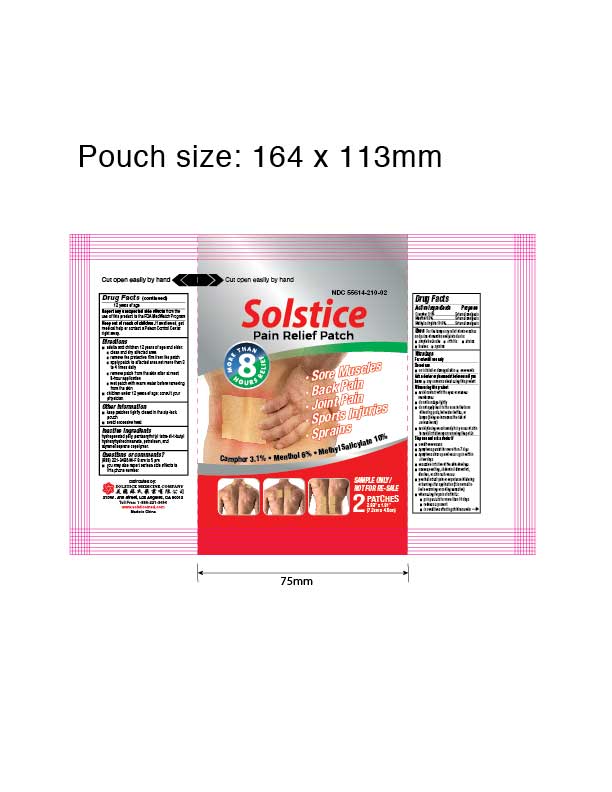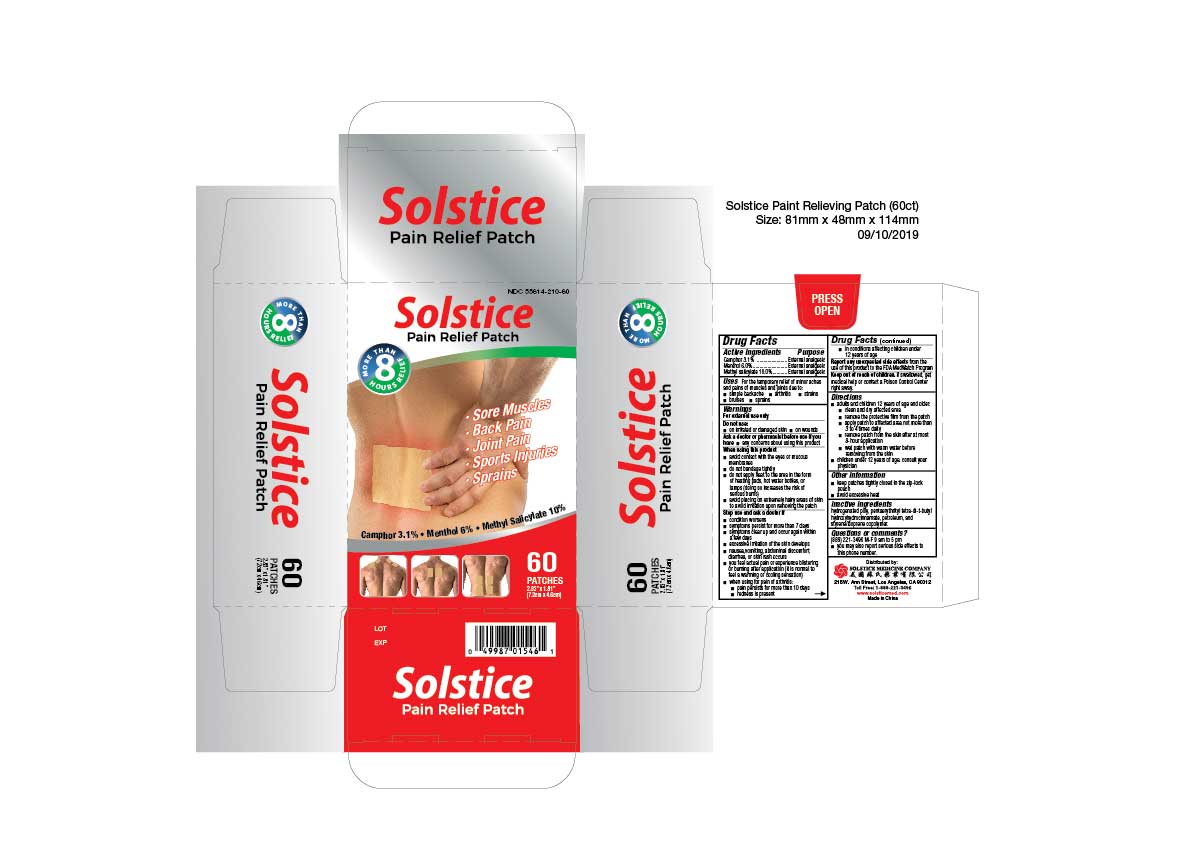 DRUG LABEL: Solstice Pain Relieving
NDC: 55614-210 | Form: PATCH
Manufacturer: MADISON ONE ACME INC
Category: otc | Type: HUMAN OTC DRUG LABEL
Date: 20251110

ACTIVE INGREDIENTS: CAMPHOR (SYNTHETIC) 3.1 g/100 g; MENTHOL 6 g/100 g; METHYL SALICYLATE 10 g/100 g
INACTIVE INGREDIENTS: HYDROGENATED POLYDECENE (550 MW); PENTAERYTHRITOL TETRAKIS(3-(3,5-DI-TERT-BUTYL-4-HYDROXYPHENYL)PROPIONATE); LIQUID PETROLEUM; STYRENE/ACRYLAMIDE COPOLYMER (MW 500000)

Drug Facts

Active ingredient
Camphor 3.1%
Menthol 6.0%
Methyl salicylate 10.0%

Purpose
External analgesic
External analgesic
External analgesic

Uses
For the temporary relief of minor aches and pains of muscles and joints due to:

- simple backache
- arthritis
- strains
- bruises
- sprains

Warnings
For external use only

Do not use
on irritated or damaged skin on wounds

Ask a doctor or pharmacist before use if you have
any concerns about using this product

When using this product

- avoid contact with the eyes or mucous membranes
- do not bandage tightly
- do not apply heat to the area in the form of heating pads, hot water bottles, or lamps (doing so increases the risk of serious burns)
- avoid placing on extremely hairy areas of skin to avoid irritation upon removing the patch

Stop use and ask a doctor if

- condition worsens
- symptoms persist for more than 7 days
- symptoms clear up and occur again within a few days
- excessive irritation of the skin develops
- nausea, vomiting, abdominal discomfort, diarrhea, or skin rash occurs
- you feel actual pain or experience blistering or burning after application (it is normal to feel a warming or cooling sensation)
- when using for pain of arthritis:
  - pain persists for more than 10 days
  - redness is present
  - in conditions affecting children under 12 years of age

ADVERSE REACTIONS

Report any unexpected side effectsfrom the use of this product to the FDA MedWatch Program

Keep out of reach of children.If swallowed, get medical help or contact a Poison Control Center right away.

Directions

- adults and children 3 years of age and older:
  - clean and dry affected area
  - remove the protective film from the patch
  - apply patch to affected area not more than 3 to 4 times daily
  - remove patch from the skin after at most 8-hour application
  - wet patch with warm water before removing from the skin

- children under 3 years of age: consult your physician

Other information

- keep patches tightly closed in the zip-lock pouch
- avoid excessive heat

INACTIVE INGREDIENT

Inactive ingredientshydrogenated poly, pentaerythrityl tetra-di-t-butyl hydroxyhydrocinnamate, petroleum, and styrene/isoprene copolymer.

Questions or comments?(888) 221-3496 M-F 9 am to 5 pm
you may also report serious side effects to this phone number

PACKAGE LABEL

Solstice Pain Relieving Patch

Camphor 3.1%, Menthol 6.0%, Methyl Salicylate 10%

NDC 55614-210-20

20 Patches, Each Patch 2.83 in x 1.81 in (7.2 cm x 4.6 cm)

PACKAGE LABEL

Solstice Pain Relieving Patch

Camphor 3.1%, Menthol 6.0%, Methyl Salicylate 10%

NDC 55614-210-60

60 Patches in 3 Pouches, 20 Patches per Pouch
Each Patch 2.83 in x 1.81 in (7.2 cm x 4.6 cm)

PACKAGE LABEL

Solstice Pain Relieving Patch

Camphor 3.1%, Menthol 6.0%, Methyl Salicylate 10%

NDC 55614-210-02

2 Patches, Each Patch 2.83 in x 1.81 in (7.2 cm x 4.6 cm)

Sample Only / Not For Re-Sale